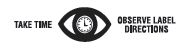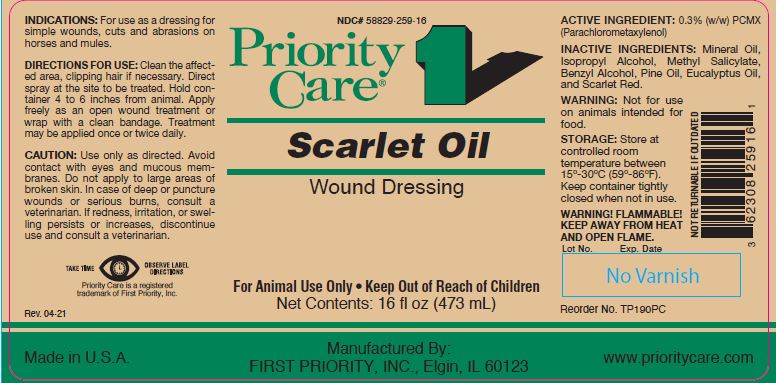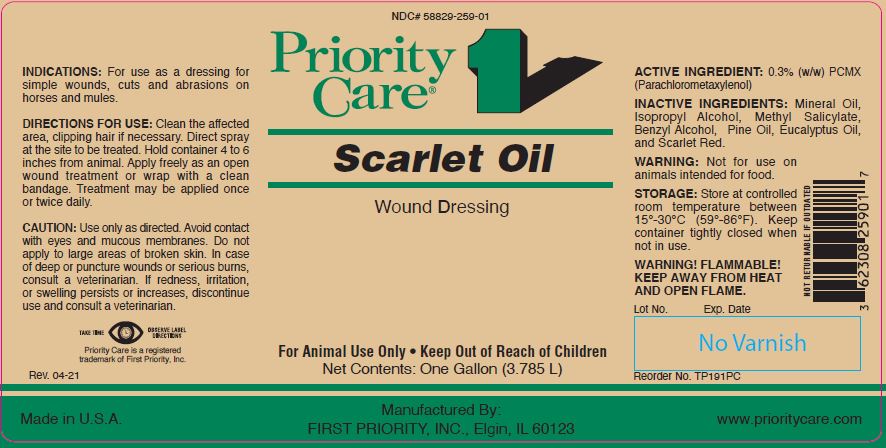 DRUG LABEL: Scarlet Oil
NDC: 58829-259 | Form: SOLUTION
Manufacturer: FIRST PRIORITY INCORPORATED
Category: animal | Type: OTC ANIMAL DRUG LABEL
Date: 20260223

ACTIVE INGREDIENTS: CHLOROXYLENOL 2.5 mg/1 mL

Scarlet Oil

PURPOSE

Wound Dressing

KEEP OUT OF REACH OF CHILDREN

For Animal Use Only • Keep Out of Reach of Children

INDICATIONS:

For use as a dressing for simple wounds, cuts and abrasions on horses and mules.

DIRECTIONS FOR USE:

Clean the affected area, clipping hair if necessary. Direct spray at the site to be treated. Hold container 4 to 6 inches from animal. Apply freely as an open wound treatment or wrap with a clean bandage. Treatment may be applied once or twice daily.

CAUTION:

Use only as directed. Avoid contact with eyes and mucous membranes. Do not apply to large areas of broken skin. In case of deep or puncture wounds or serious burns, consult a veterinarian. If redness, irritation, or swelling persists or increases, discontinue use and consult a veterinarian.

ACTIVE INGREDIENT:

0.3% (w/w) PCMX (Parachlorometaxylenol)

INACTIVE INGREDIENTS:

Mineral Oil, Isopropyl Alcohol, Methyl Salicylate, Benzyl Alcohol, Pine Oil, Eucalyptus Oil, and Scarlet Red.

WARNING:

Not for use on animals intended for food.

STORAGE:

Store at controlled room temperature between 15º-30ºC (59º-86ºF). Keep container tightly closed when not in use.

WARNINGS AND PRECAUTIONS

WARNING! FLAMMABLE! KEEP AWAY FROM HEAT AND OPEN FLAME.

Net Contents:

16 fl oz (473 mL) Reorder No. TP190PC

One Gallon (3.785 L) Reorder No. TP191PC

INFORMATION FOR OWNERS/CAREGIVERS

Priority Care is a registered trademark of First Priority, Inc.

Manufactured By: FIRST PRIORITY, INC., Elgin, IL 60123-1146

NOT RETURNABLE IF OUTDATED